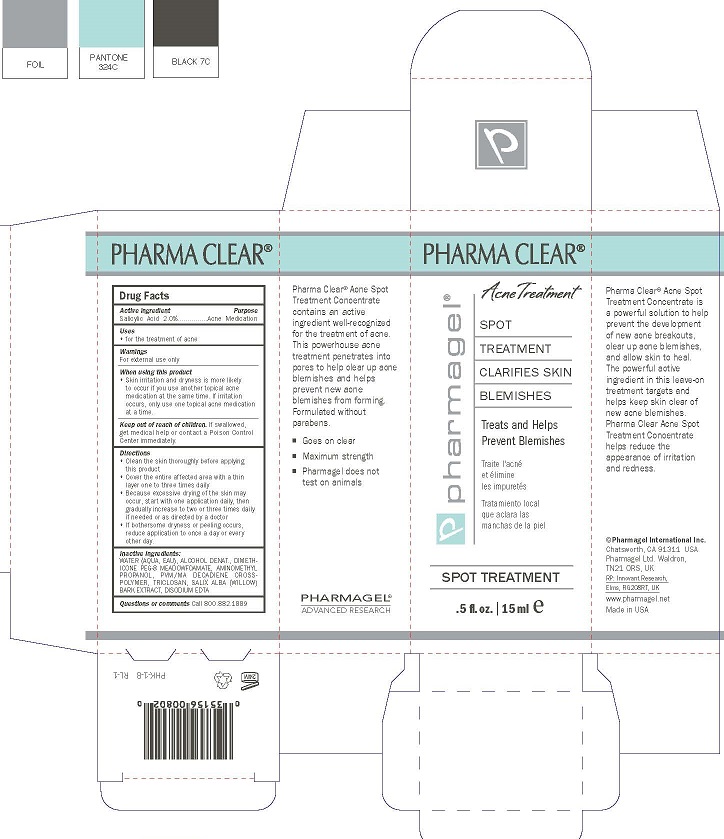 DRUG LABEL: PHARMA CLEAR SPOT TREATMENT
NDC: 67879-104 | Form: LIQUID
Manufacturer: PHARMAGEL INTERNATIONAL INC
Category: otc | Type: HUMAN OTC DRUG LABEL
Date: 20260219

ACTIVE INGREDIENTS: SALICYLIC ACID 2 g/100 mL
INACTIVE INGREDIENTS: WATER; ALCOHOL; DIMETHICONE PEG-8 LAURATE; AMINOMETHYLPROPANOL; COPOVIDONE K25-31; SALIX NIGRA BARK; EDETATE DISODIUM

PHARMAGEL - PHARMA CLEAR SPOT TREATMENT (67879-104)

ACTIVE INGREDIENTS

Salicylic Acid 2.0%

PURPOSE

Acne Medication

Uses

Use for treatment of acne and to decrease bacteria on the skin.

WARNINGS

For external use only

When using this product:

• avoid contact with the eyes. If product gets into the eyes, rinse thoroughly with water.

• Using other topical acne medications at the same time or immediately following use of this product may increase dryness or irritation of the

skin. If this occurs, only one medication should be used unless directed by a doctor.

• Limit use to the face and neck.

Keep out of reach of children. If swallowed, get medical help or contact a Poison Control Center immediately.

DIRECTIONS:

Apply sparingly to blemishes after cleansing. Allow to penetrate and dry before applying other preparations. For best results,

use twice daily.

INACTIVE INGREDIENTS:

WATER (AQUA), ALCOHOL DENAT, DIMETHICONE PEG-8 MEADOWFOAMATE, AMINOMETHYL PROPANOL, PVM/MA DECADIENE CROSSPOLYMER, TRICLOSAN, SALIX NIGRA (WILLOW) BARK EXTRACT, DISODIUM EDTA